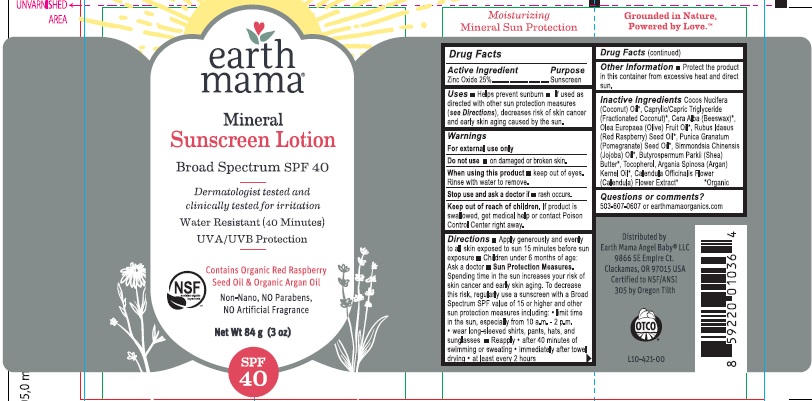 DRUG LABEL: SUNSCREEN
NDC: 62932-169 | Form: OINTMENT
Manufacturer: Private Label Select Ltd CO
Category: otc | Type: HUMAN OTC DRUG LABEL
Date: 20181102

ACTIVE INGREDIENTS: ZINC OXIDE 25 g/100 g
INACTIVE INGREDIENTS: PUNICA GRANATUM SEED OIL; COCONUT OIL; CAPRYLIC/CAPRIC/LAURIC TRIGLYCERIDE; YELLOW WAX; RASPBERRY SEED OIL; SIMMONDSIA CHINENSIS SEED WAX; SHEA BUTTER; TOCOPHEROL; ARGAN OIL; CALENDULA OFFICINALIS FLOWER; OLEA EUROPAEA FRUIT VOLATILE OIL

earthmama Mineral Suncreen SPF40 Lotion